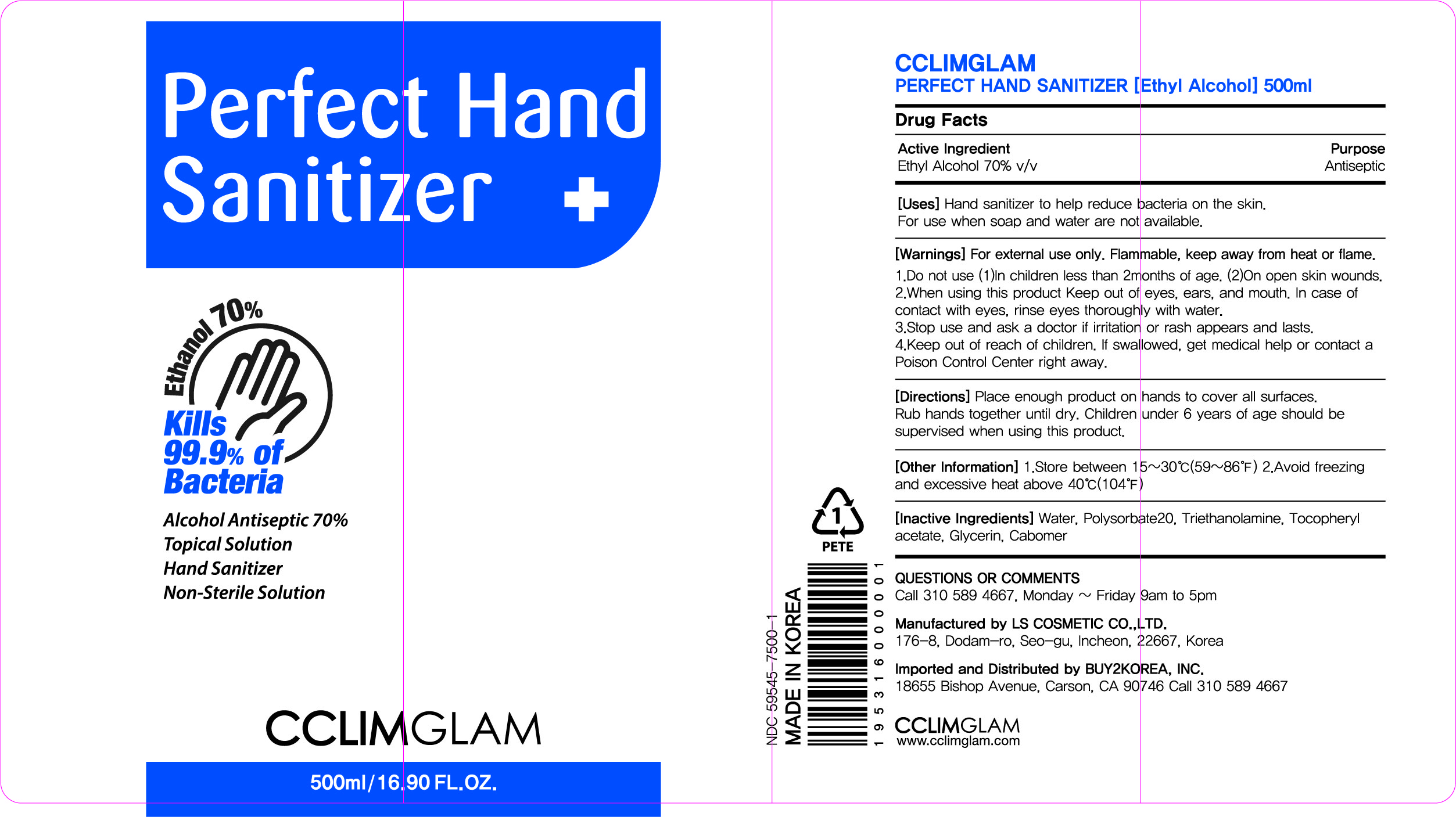 DRUG LABEL: CCLIMGLAM Perfect Hand Sanitizer
NDC: 59545-7500 | Form: GEL
Manufacturer: LS COSMETIC CO.,LTD.
Category: otc | Type: HUMAN OTC DRUG LABEL
Date: 20200515

ACTIVE INGREDIENTS: ALCOHOL 350 mL/500 mL
INACTIVE INGREDIENTS: ALPHA-TOCOPHEROL ACETATE; GLYCERIN; CARBOMER HOMOPOLYMER, UNSPECIFIED TYPE; WATER; TROLAMINE; POLYSORBATE 20

HANBAEG PRODUCT
CCLIMGLAM Perfect Hand Sanitizer (500 mL) : 59545-7500